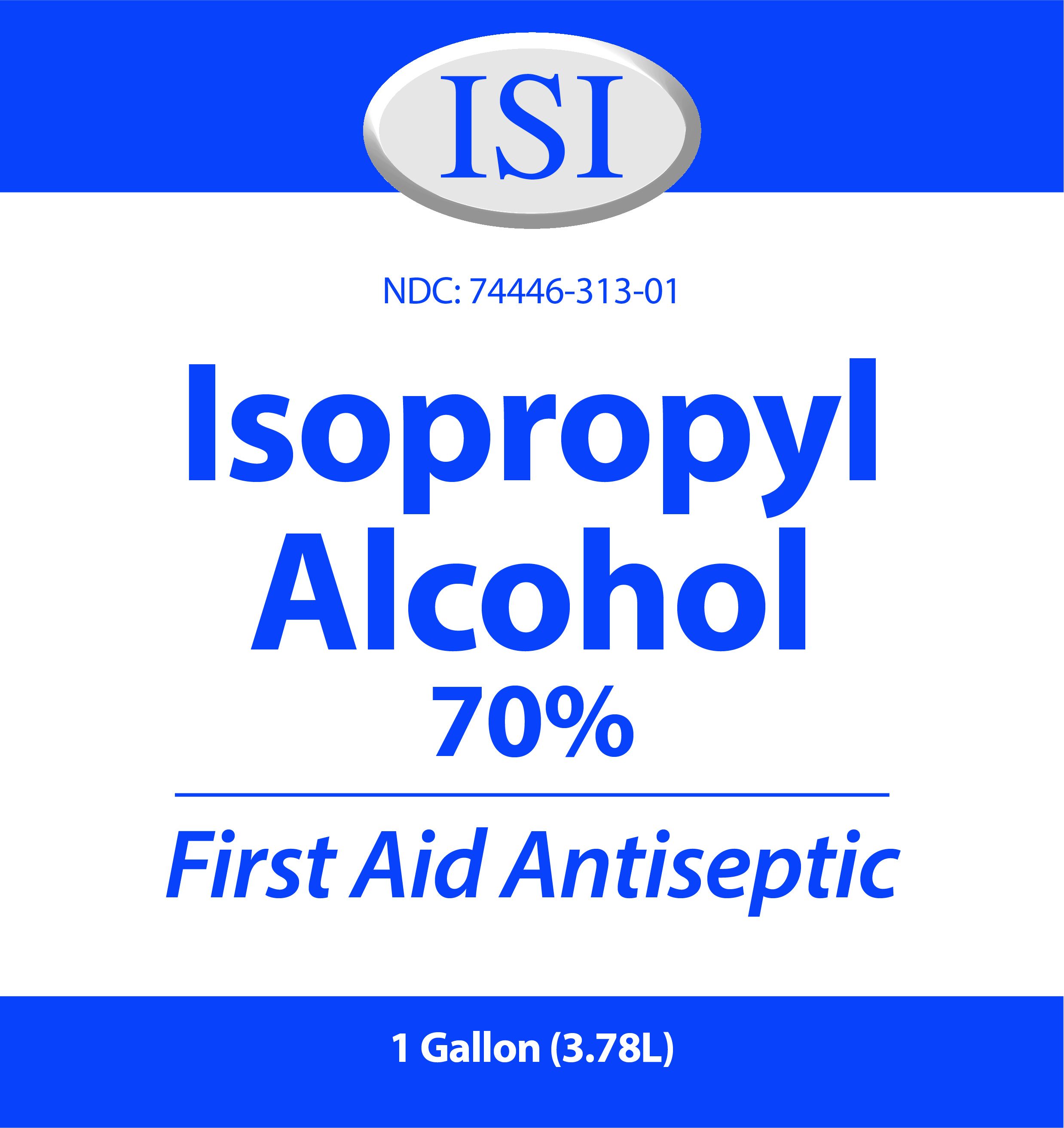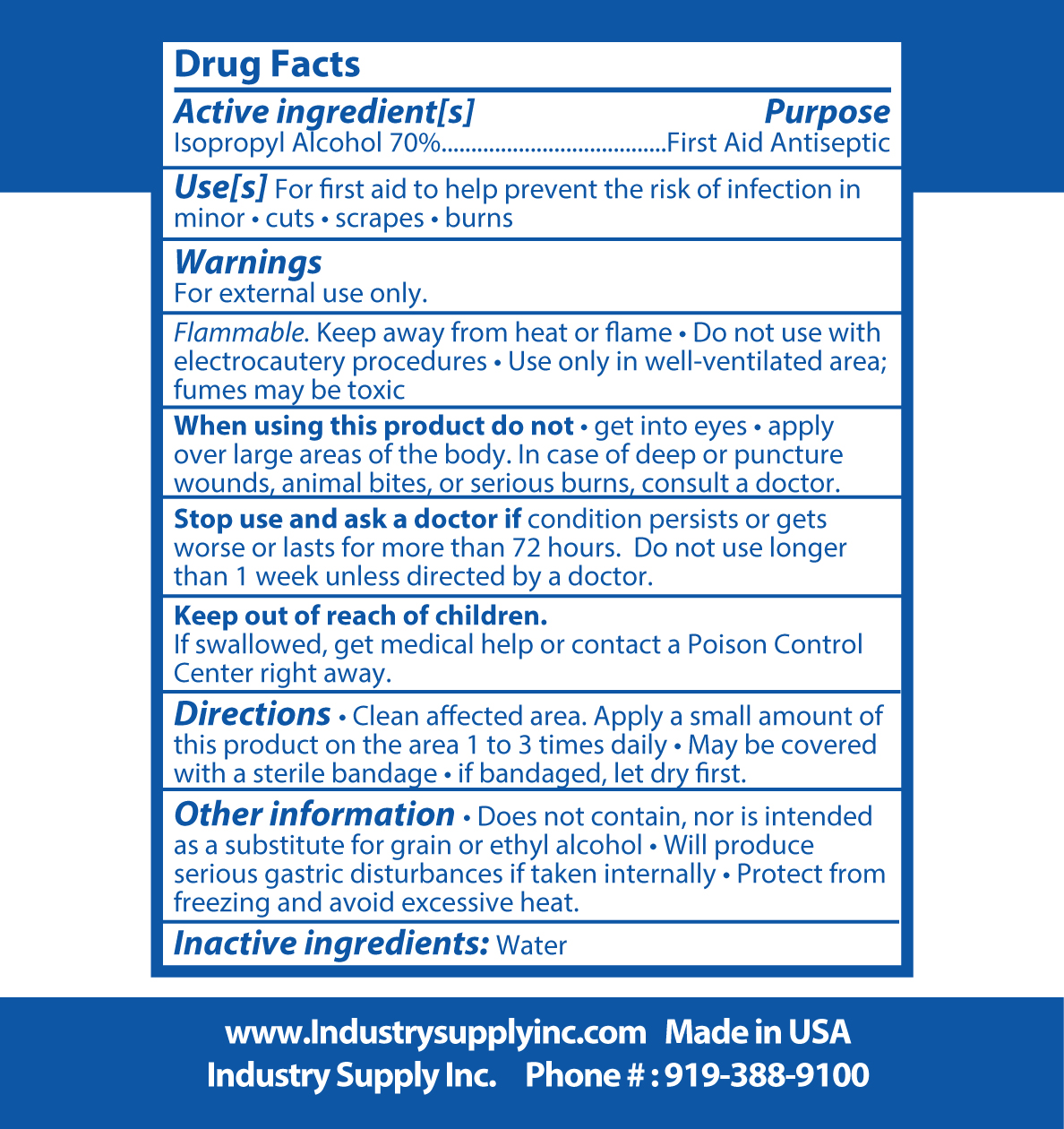 DRUG LABEL: ISOPROPYL ALCOHOL 70%
NDC: 74446-313 | Form: LIQUID
Manufacturer: INDUSTRY SUPPLY INC
Category: otc | Type: HUMAN OTC DRUG LABEL
Date: 20200603

ACTIVE INGREDIENTS: ISOPROPYL ALCOHOL 70 L/100 L
INACTIVE INGREDIENTS: WATER 30 L/100 L

Isopropyl Alcohol 70%

This is Isopropyl Alcohol 70% USP.

We are just relabeling this product.

It is made with only the following:

Isopropyl Alcohol USP or Food Chemical Codex (FCC) Grade) 70% Volume/Volume

Sterile, distilled, or boiled cold water

The firm does not add other active or inactive ingredients. Different or additonal ingredients may impace the quality and potency of the product.

ACTIVE INGREDIENT

Alcohol 70% v/v Purpose:Antiseptic

PURPOSE

Antiseptic: For first adi to help prevent the risk of infection in minor cuts, scrapes, or burns.

INDICATIONS AND USAGE

For First Aid to help prevent the risk of infection in minor cuts, scrapes, and burns.

WARNINGS

For external use only. Flammable. Keep away from flame.

When using this product do not get into eyes, apply over large areas of the body. In case of deep or puncture wounds, animal bites, or serious burns, consult a doctor.

Stop use and ask a doctor if condition persists or gets worse or lasts for for more than 72 hours. Do not use longer than 1 week unless directed by a doctor.

Keep out of reach of children, if swallowed get medical help or contact a Poison Control Center right away.

DOSAGE AND ADMINISTRATION

Clean affected area. Apply a small amount of this product on the area 1 to 3 times daily. May be covered with a sterile bandage. If bandaged, let dry first.

STORAGE AND HANDLING

Does not contain, nor is inteded as a subsitutire for grain or ethyl alcohol. Will produce serious gastric disturbances if taken internally. Protect from freezing and avoid excessive heat.

INACTIVE INGREDIENT

Purified Water USP